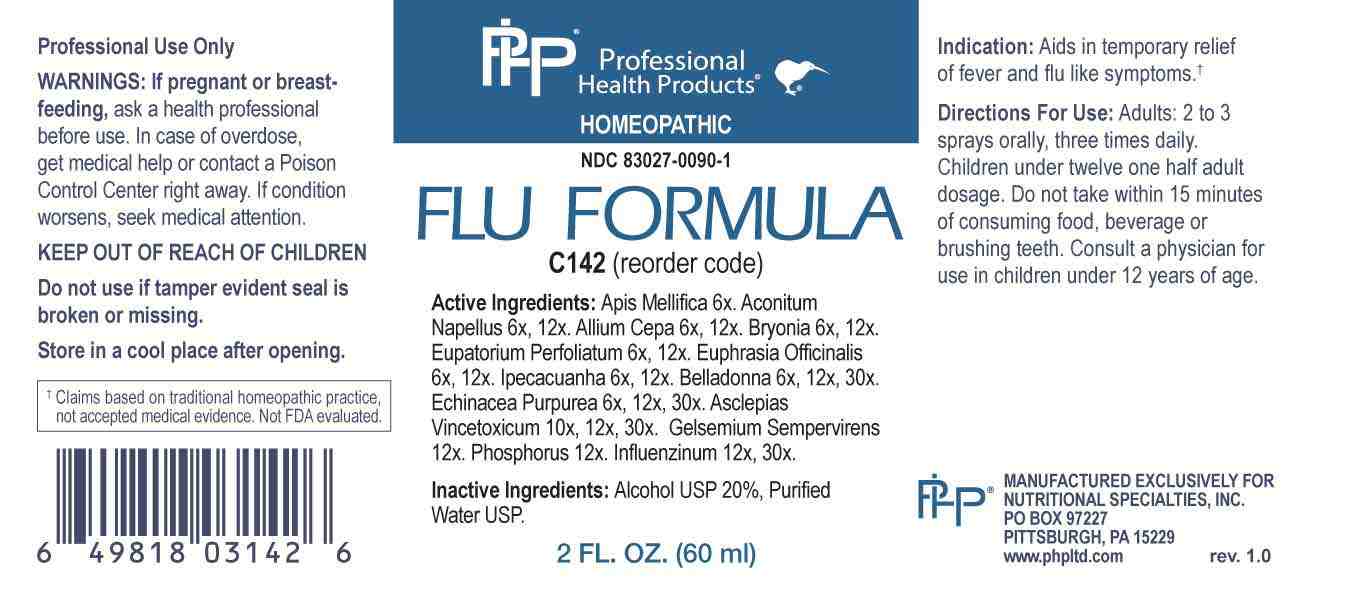 DRUG LABEL: Flu Formula
NDC: 83027-0090 | Form: SPRAY
Manufacturer: Nutritional Specialties, Inc.
Category: homeopathic | Type: HUMAN OTC DRUG LABEL
Date: 20230627

ACTIVE INGREDIENTS: APIS MELLIFERA 6 [hp_X]/1 mL; ACONITUM NAPELLUS WHOLE 6 [hp_X]/1 mL; ONION 6 [hp_X]/1 mL; BRYONIA ALBA ROOT 6 [hp_X]/1 mL; EUPATORIUM PERFOLIATUM FLOWERING TOP 6 [hp_X]/1 mL; EUPHRASIA STRICTA 6 [hp_X]/1 mL; IPECAC 6 [hp_X]/1 mL; ATROPA BELLADONNA 6 [hp_X]/1 mL; ECHINACEA PURPUREA WHOLE 6 [hp_X]/1 mL; VINCETOXICUM HIRUNDINARIA ROOT 10 [hp_X]/1 mL; GELSEMIUM SEMPERVIRENS ROOT 12 [hp_X]/1 mL; PHOSPHORUS 12 [hp_X]/1 mL; INFLUENZA A VIRUS A/VICTORIA/2570/2019 IVR-215 (H1N1) ANTIGEN (UV, FORMALDEHYDE INACTIVATED) 12 [hp_X]/1 mL; INFLUENZA A VIRUS A/DARWIN/9/2021 IVR-228 (H3N2) ANTIGEN (UV, FORMALDEHYDE INACTIVATED) 12 [hp_X]/1 mL; INFLUENZA B VIRUS B/AUSTRIA/1359417/2021 BVR-26 ANTIGEN (UV, FORMALDEHYDE INACTIVATED) 12 [hp_X]/1 mL; INFLUENZA B VIRUS B/PHUKET/3073/2013 ANTIGEN (UV, FORMALDEHYDE INACTIVATED) 12 [hp_X]/1 mL
INACTIVE INGREDIENTS: WATER; ALCOHOL

DRUG FACTS:

ACTIVE INGREDIENTS:

Apis Mellifica 6X, Aconitum Napellus 6X, 12X, Allium Cepa 6X, 12X, Bryonia 6X, 12X, Eupatorium Perfoliatum 6X. 12X, Euphrasia Officinalis 6X, 12X, Ipecacuanha 6X, 12X, Belladonna 6X, 12X, 30X, Echinacea Purpurea 6X, 12X, 30X, Asclepias Vincetoxicum 10X, 12X, 30X, Gelsemium Sempervirens 12X, Phosphorus 12X, Influenzinum 12X, 30X.

PURPOSE:

Aids in temporary relief of fever and flu like symptoms.†

†Claims based on traditional homeopathic practice, not accepted medical evidence. Not FDA evaluated.

WARNINGS:

Professional Use Only

If pregnant or breast-feeding, ask a health professional before use.

In case of overdose, get medical help or contact a Poison Control Center right away.

If condition worsens, seek medical attention.

KEEP OUT OF REACH OF CHILDREN

Do not use if tamper evident seal is broken or missing.

Store in a cool place after opening

KEEP OUT OF REACH OF CHILDREN:

In case of overdose, get medical help or contact a Poison Control Center right away.

DIRECTIONS:

Adults: 2 to 3 sprays orally, three times daily. Children under twelve one half adult dosage. Do not take within 15 minutes of consuming food, beverage or brushing teeth. Consult a physician for use in children under 12 years of age.

INDICATIONS:

Aids in temporary relief of fever and flu like symptoms.†

†Claims based on traditional homeopathic practice, not accepted medical evidence. Not FDA evaluated.

INACTIVE INGREDIENTS:

Alcohol USP 20%, Purified Water USP.

QUESTIONS:

MANUFACTURED EXCLUSIVELY FOR

NUTRITIONAL SPECIALTIES, INC.

PO BOX 97227

PITTSBURG, PA 15229

www.phpltd.com

PACKAGE LABEL DISPLAY:

Professional

Health Products

HOMEOPATHIC

NDC 83027-0090-1

FLU FORMULA

2 FL. OZ (60 ml)